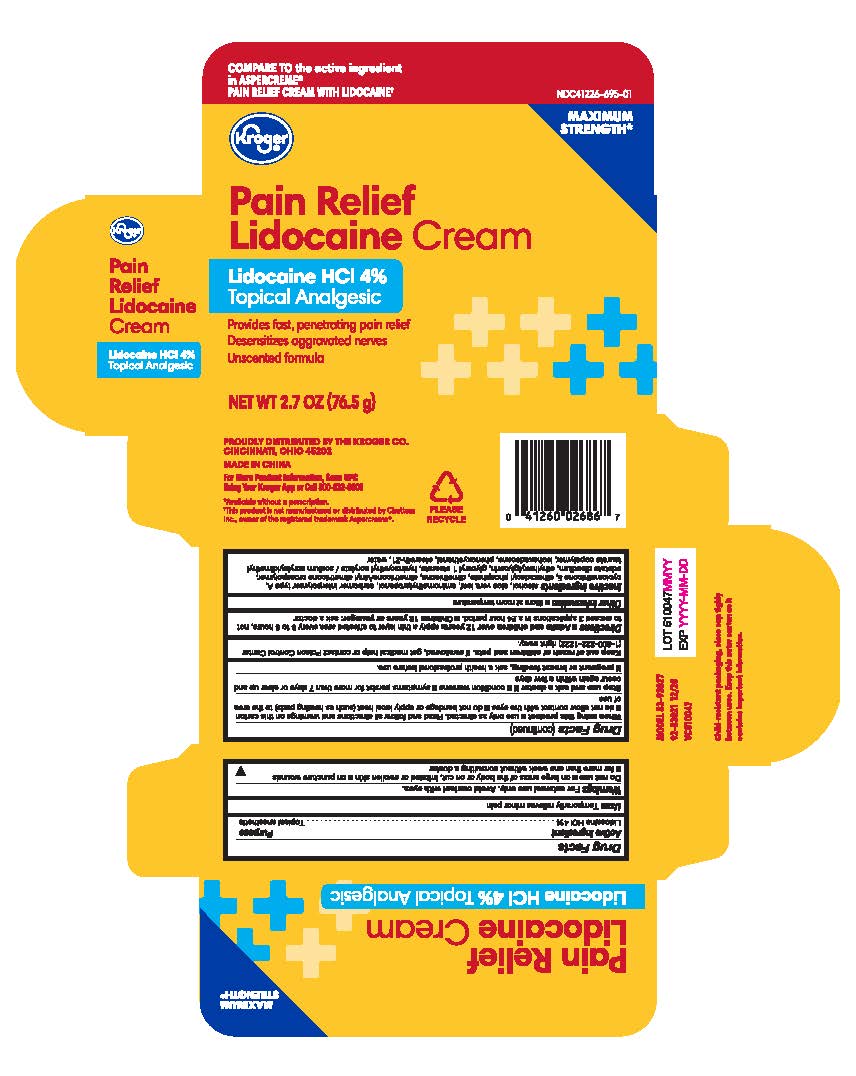 DRUG LABEL: Pain Relief Lidocaine
NDC: 41226-695 | Form: CREAM
Manufacturer: Kroger Company
Category: otc | Type: HUMAN OTC DRUG LABEL
Date: 20260209

ACTIVE INGREDIENTS: LIDOCAINE 4 g/100 g
INACTIVE INGREDIENTS: HYDROXYETHYL ACRYLATE/SODIUM ACRYLOYLDIMETHYL TAURATE COPOLYMER (45000 MPA.S AT 1%); PHENOXYETHANOL; ALOE VERA LEAF; AMINOMETHYLPROPANOL; ISOHEXADECANE; DIHEXADECYL PHOSPHATE; CARBOMER INTERPOLYMER TYPE A (55000 CPS); CYCLOMETHICONE 5; DIMETHICONE/VINYL DIMETHICONE CROSSPOLYMER (SOFT PARTICLE); EDETATE DISODIUM ANHYDROUS; ETHYLHEXYLGLYCERIN; WATER; DIMETHICONE; GLYCERYL 1-STEARATE; ALCOHOL; STEARETH-21

Kroger Pain Relief Lidocaine Cream

Active Ingredient

Lidocaine HCl 4%

Purpose

Topical anesthetic

Uses

Temporarily relieves minor pain

Warnings

For external use only. Avoid contact with eyes.

Do not use

- on a large areas of the body or on cut, irritated or swollen skin
- on punture wounds
- for more than one week without consulting a doctor

Stop use and ask a doctor if

- condition worsens
- symptoms persist for more than 7 days or clear up and occur again within a few days

If pregnant or breast feeding,

ask a health professional before use

Keep out of reach of children and pets

If swallowed, get medical help or contact Poison Control Center (1-800-222-1222) right away.

Directions

- adults and childrens over 12 years: apply a thin layer to affected area every 6 to 8 hours, not to exceed 3 applications in a 24 hour period.
- Children 12 years or younger: ask a doctor

Other

Store at room temperature

Inactive Ingredients

alcohol, aloe vera leaf, aminomethylpropanol, carbomer interpolymer type A, cyclomethicone 5, dihexadeycl phosphete, dimeticone, dimeticone/vinyl dimeticone crosspolymer, edetate disosium, ethylhexylglycerin, glyceryl 1 stearate, hydroxyethyl acrylate/sodium acryloyldimethyl taurate copolymer, isohexadecane, phenoxyethanol, steareth-21, water.